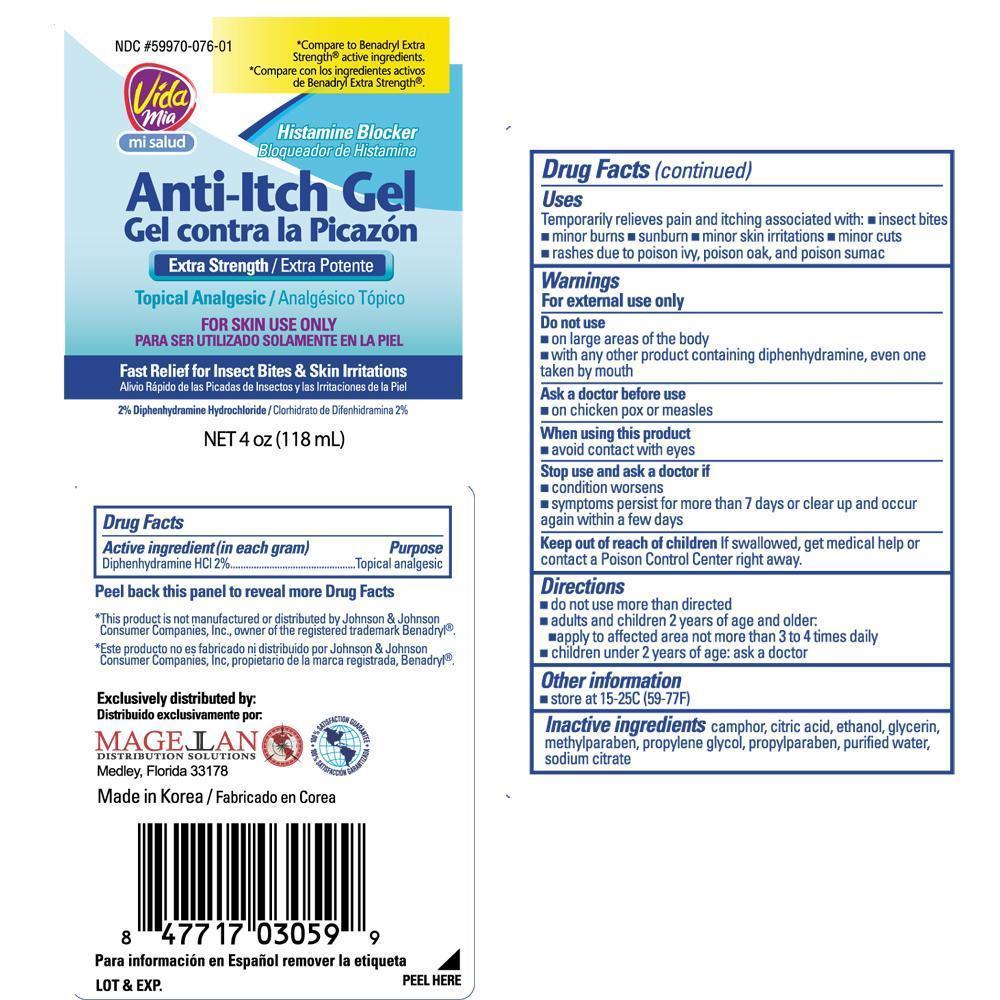 DRUG LABEL: Anti-Itch
NDC: 59970-076 | Form: GEL
Manufacturer: Navarro Discount Pharmacies,LLC
Category: otc | Type: HUMAN OTC DRUG LABEL
Date: 20130118

ACTIVE INGREDIENTS: DIPHENHYDRAMINE HYDROCHLORIDE 2 g/100 g
INACTIVE INGREDIENTS: CAMPHOR (SYNTHETIC); CITRIC ACID MONOHYDRATE; ALCOHOL; GLYCERIN; METHYLPARABEN; PROPYLENE GLYCOL; PROPYLPARABEN; WATER; SODIUM CITRATE

Drug Facts

Active ingredients (in each gram)

Diphenhydramine HCl 2%

Purposes

Topical analgesic

Skin protectant

Uses

- temporarily relieves itching and pain associated with insect bites, minor skin irritations and rashes due to poison ivy, poison oak or poison sumac
- dries the oozing and weeping of poison ivy, poison oak, and poison sumac

Warnings

For external use only

Do not use

- on chicken pox or measles
- with any other product containing diphenhydramine, even one taken by mouth
- on large areas of the body, including large areas of poison ivy, sunburn, or broken, blistered or oozing skin

Stop use and ask a doctor if

- condition worsens or does not improve within 7 days
- symptoms persist for more than 7 days or clear up and occur again within a few days

Keep out of reach of children

If swallowed, get medical help or contact a Poison Control Center right away

Directions

- adults and children 12 years of age and over: apply to affected area not more than 3 to 4 times daily
- children under 12 years of age: ask a doctor
- do not use more often than directed

Other information

- store at 15°-25°C (59°-77°F)

Inactive ingredients

camphor, citric acid, ethanol, glycerin, methylparaben, propylene glycol, propylparaben, purified water, sodium citrate

Package label

Anti-Itch Gel